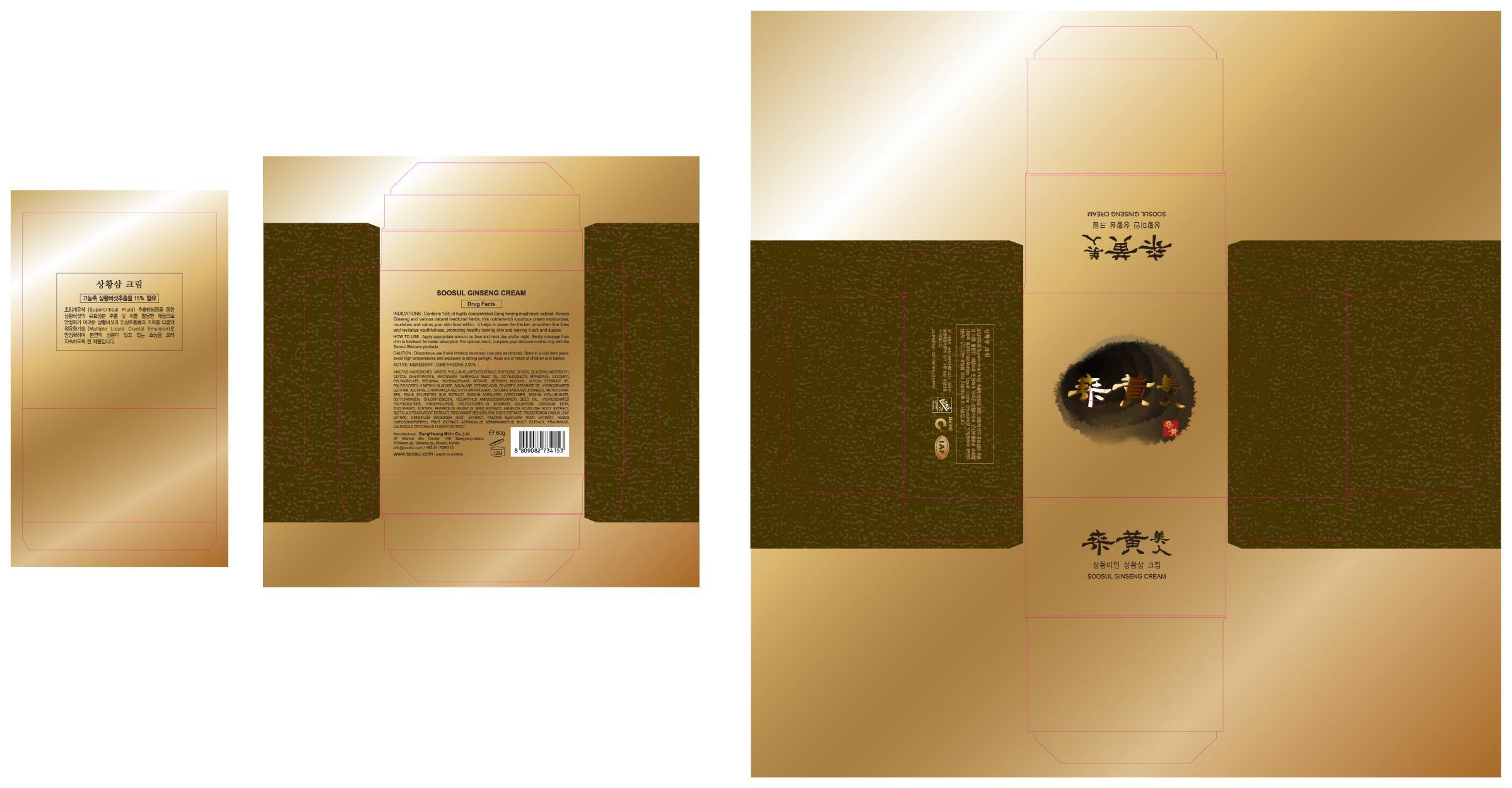 DRUG LABEL: SOOSUL GINSENG
NDC: 69351-020 | Form: CREAM
Manufacturer: Sang Hwang Mi-in Co., Ltd.
Category: otc | Type: HUMAN OTC DRUG LABEL
Date: 20141127

ACTIVE INGREDIENTS: DIMETHICONE 1.2 g/60 g
INACTIVE INGREDIENTS: WATER; BUTYLENE GLYCOL

ACTIVE INGREDIENT

Active Ingredient: DIMETHICONE 2.00%

INACTIVE INGREDIENT

Inactive Ingredients:
WATER, PHELLINUS LINTEUS EXTRACT, BUTYLENE GLYCOL, GLYCERIN, NEOPENTYL GLYCOL DIHEPTANOATE, MACADAMIA TERNIFOLIA SEED OIL, OCTYLDODECYL MYRISTATE, GLYCERYL POLYACRYLATE, BEESWAX, ISOHEXADECANE, BETAINE, CETEARYL ALCOHOL, GLYCOL STEARATE SE, POLYGLYCERYL-3 METHYLGLUCOSE, SQUALANE, STEARIC ACID, GLYCERYL STEARATE SE, HYDROGENATED LECITHIN, ALCOHOL, CHAMOMILLA RECUTITA (MATRICARIA), CUCUMIS SATIVUS(CUCUMBER), METHYLPARABEN, PINUS SYLVESTRIS BUD EXTRACT, SODIUM ACRYLATES COPOLYMER, SODIUM HYALURONATE, BUTYLPARABEN, CHLORPHENESIN, HELIANTHUS ANNUUS(SUNFLOWER) SEED OIL, HYDROGENATED POLYISOBUTENE, PHOSPHOLIPIDS, POLYGLYCERYL-10 STEARATE, ALLANTOIN, DISODIUM EDTA, TOCOPHERYL ACETATE, PHASEOLUS RADIATUS SEED EXTRACT, ANGELICA ACUTILOBA ROOT EXTRACT, BLETILLA STRIATA ROOT EXTRACT, TRICHOSANTHES KIRILOWII ROOT EXTRACT, POGOSTEMON CABLIN LEAF EXTRAC, CIMICIFUGA RACEMOSA ROOT EXTRACT, PAEONIA ALBIFLORA ROOT EXTRACT, RUBUS IDAEUS(RASPBERRY) FRUIT EXTRACT, ASTRAGALUS MEMBRANACEUS ROOT EXTRACT, FRAGRANCE, CALENDULA OFFICINALIS FLOWER EXTRACT

PURPOSE

PURPOSE: SKIN PROTECTANT

Caution

Caution: Discontinue use if skin irritation develops. Use only as directed. Store in a cool dark place, avoid high temperatures and exposure to strong sunlight. Keep out of reach of children and babies.

Keep out of reach of children and babies.

Indications

Contains 15% of highly concentrated Sang-hwang mushroom extract, Korean Ginseng and various natural medicinal herbs, this nutrient-rich luxurious cream moisturizes, nourishes and calms your skin from within. It helps to erase the freckle, smoothen fine lines and revitalize youthfulness, promoting healthy looking skin and leaving it soft and supple.

How to use: Apply appropriate amount on face and neck day and/or night. Gently massage from chin to forehead for better absorption. For optimal result, complete your skincare routine only with the Soosul Skincare products.